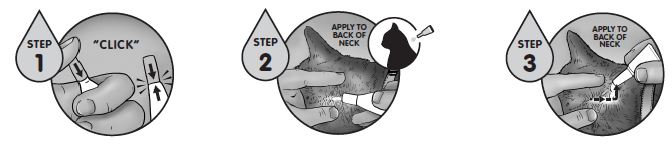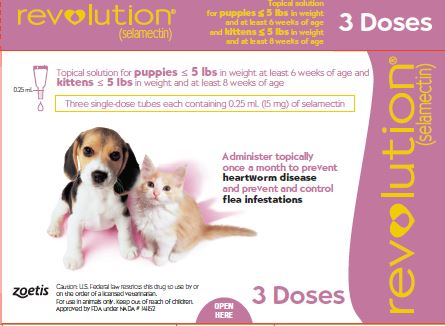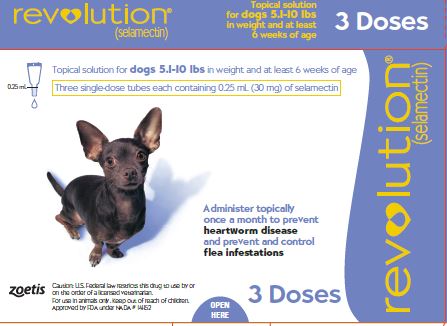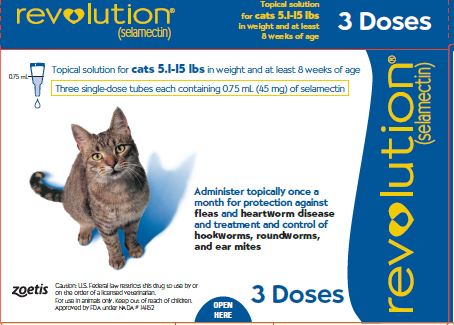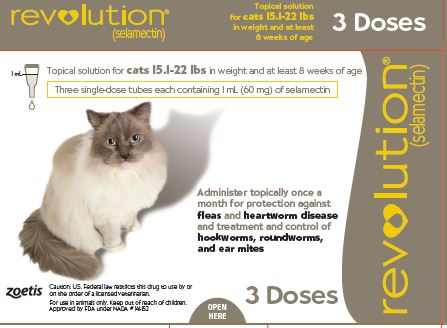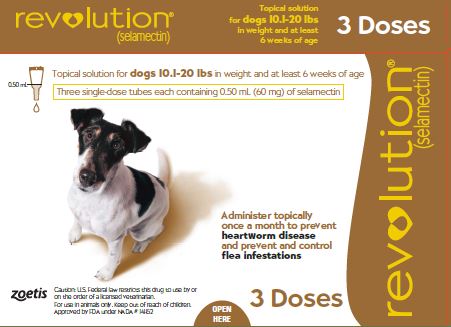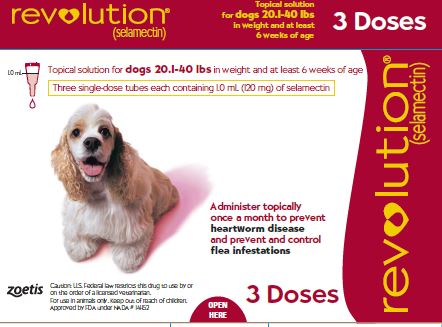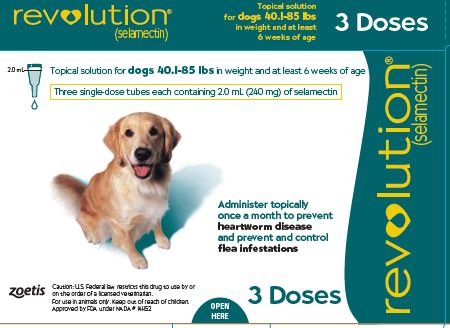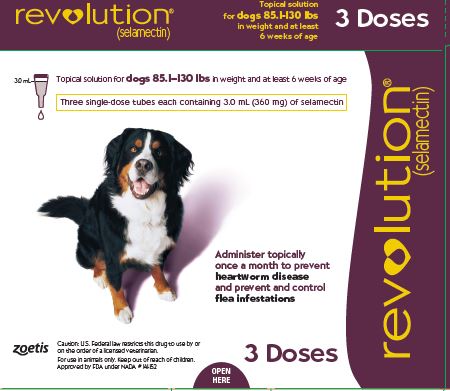 DRUG LABEL: REVOLUTION
NDC: 54771-9661 | Form: SOLUTION
Manufacturer: Zoetis Inc.
Category: animal | Type: PRESCRIPTION ANIMAL DRUG LABEL
Date: 20241211

ACTIVE INGREDIENTS: SELAMECTIN 60 mg/1 mL
INACTIVE INGREDIENTS: ISOPROPYL ALCOHOL; BUTYLATED HYDROXYTOLUENE

REVOLUTION® (selamectin)

REVOLUTION® (selamectin)
Topical Parasiticide For Dogs and Cats

CAUTION

US Federal law restricts this drug to use by or on the order of a licensed veterinarian.

DESCRIPTION

Revolution (selamectin) Topical Parasiticide is available as a colorless to yellow, ready to use solution in single dose tubes for topical (dermal) treatment of dogs six weeks of age and older and cats eight weeks of age and older. The content of each tube is formulated to provide a minimum of 2.7 mg/lb (6 mg/kg) of body weight of selamectin. The chemical composition of selamectin is (5Z,25S)-25-cyclohexyl-4'-O-de(2,6-dideoxy-3-O-methyl-α-L-arabino-hexopyranosyl)-5-demethoxy-25-de(1-methylpropyl)-22,23-dihydro-5-hydroxyiminoavermectin A1a.

INDICATIONS

Revolution is recommended for use in dogs six weeks of age or older and cats eight weeks of age and older for the following parasites and indications:

Dogs:

Revolution kills adult fleas and prevents flea eggs from hatching for one month and is indicated for the prevention and control of flea infestations (Ctenocephalides felis), prevention of heartworm disease caused by Dirofilaria immitis, and the treatment and control of ear mite (Otodectes cynotis) infestations. Revolution also is indicated for the treatment and control of sarcoptic mange (Sarcoptes scabiei) and for the control of tick infestations due to Dermacentor variabilis.

Cats:

Revolution kills adult fleas and prevents flea eggs from hatching for one month and is indicated for the prevention and control of flea infestations (Ctenocephalides felis), prevention of heartworm disease caused by Dirofilaria immitis, and the treatment and control of ear mite (Otodectes cynotis) infestations. Revolution is also indicated for the treatment and control of roundworm (Toxocara cati) and intestinal hookworm (Ancylostoma tubaeforme) infections in cats.

DOSAGE AND ADMINISTRATION

The recommended minimum dose is 2.7 mg selamectin per pound (6 mg/kg) of body weight.
Administer the entire contents of a single dose tube (or two tubes used in combination for dogs weighing over 130 pounds) of Revolution topically in accordance with the following tables.

Cats (lb) | Package color | mg per tube | Potency (mg/mL) | Administered volume (mL)
Up to 5 | Mauve | 15 mg | 60 | 0.25
5.1–15 | Blue | 45 mg | 60 | 0.75
15.1–22 | Taupe | 60 mg | 60 | 1.0

For cats over 22 lbs use the appropriate combination of tubes.

Dogs (lb) | Package color | mg per tube | Potency (mg/mL) | Administered volume (mL)
Up to 5 | Mauve | 15 mg | 60 | 0.25
5.1–10 | Purple | 30 mg | 120 | 0.25
10.1–20 | Brown | 60 mg | 120 | 0.5
20.1–40 | Red | 120 mg | 120 | 1.0
40.1–85 | Teal | 240 mg | 120 | 2.0
85.1–130 | Plum | 360 mg | 120 | 3.0

For dogs over 130 lbs use the appropriate combination of tubes.

Recommended for use in dogs 6 weeks of age and older and in cats 8 weeks of age and older.

A veterinarian or veterinary technician should demonstrate or instruct the pet owner regarding the appropriate technique for applying Revolution topically to dogs and cats prior to first use.

Firmly press the cap down to puncture the seal on the Revolution tube; a clicking sound will confirm that the cap has successfully punctured the seal. Remove the cap and check to ensure that the tip of the tube is open. To administer the product, part the hair on the back of the animal at the base of the neck in front of the shoulder blades until the skin is visible. Place the tip of the tube on the skin and squeeze the tube 3 or 4 times to empty its entire contents directly onto the skin in one spot. Keeping the tube squeezed, drag it away from the liquid and lift to remove. Check the tube to ensure that it is empty.
Do not massage the product into the skin. Due to alcohol content, do not apply to broken skin. Avoid contact between the product and fingers. Do not apply when the haircoat is wet. Bathing or shampooing the dog 2 or more hours after treatment will not reduce the effectiveness of Revolution against fleas or heartworm. Bathing or shampooing the cat 2 hours after treatment will not reduce the effectiveness of Revolution against fleas. Bathing or shampooing the cat 24 hours after treatment will not reduce the effectiveness of Revolution against heartworm. Stiff hair, clumping of hair, hair discoloration, or a slight powdery residue may be observed at the treatment site in some animals. These effects are temporary and do not affect the safety or effectiveness of the product. Discard empty tubes in your ordinary household refuse.

DOSAGE AND ADMINISTRATION continued

Flea Control in Dogs and Cats

For the prevention and control of flea infestations, Revolution should be administered at monthly intervals throughout the flea season, starting one month before fleas become active. In controlled laboratory studies >98% of fleas were killed within 36 hours. Results of clinical field studies using Revolution monthly demonstrated >90% control of flea infestations within 30 days of the first dose. Dogs and cats treated with Revolution, including those with pre-existing flea allergy dermatitis, showed improvement in clinical signs associated with fleas as a direct result of eliminating the fleas from the animals and their environment.

If the dog or cat is already infested with fleas when the first dose of Revolution is administered, adult fleas on the animal are killed and no viable fleas hatch from eggs after the first administration. However, an environmental infestation of fleas may persist for a short time after beginning treatment with Revolution because of the emergence of adult fleas from pupae.

Heartworm Prevention in Dogs and Cats

For the prevention of heartworm disease, Revolution must be administered on a monthly basis. Revolution may be administered year-round or at least within one month after the animal's first exposure to mosquitoes and monthly thereafter until the end of the mosquito season. The final dose must be given within one month after the last exposure to mosquitoes. If a dose is missed and a monthly interval between dosing is exceeded then immediate administration of Revolution and resumption of monthly dosing will minimize the opportunity for the development of adult heartworms. When replacing another heartworm preventive product in a heartworm disease prevention program, the first dose of Revolution must be given within a month of the last dose of the former medication.

Selamectin, the active ingredient in Revolution, is a macrocyclic lactone compound. These compounds effectively prevent the development of adult heartworms when administered to dogs and cats within one month of exposure to infective (L3) Dirofilaria immitis larvae. Efficacy of macrocyclic lactones decreases below 100% in dogs, however, if first administered >2 months after exposure to infective larvae. Thus, in heartworm endemic regions, delaying initiation of heartworm prevention using Revolution beyond 2 months of first exposure to infective larvae (e.g., starting puppies and kittens at >8 weeks of age), or gaps of >2 months in the administration of Revolution during periods of heartworm transmission, increases the risk of the animal acquiring heartworms. Animals with unknown heartworm history that test negative for heartworms prior to the initiation of Revolution may be harboring pre-patent infections at the time Revolution was started. Testing such animals 3–4 months after initiation of Revolution would be necessary to confirm their negative heartworm status.

At the discretion of the veterinarian, cats ≥6 months of age may be tested to determine the presence of existing heartworm infections before beginning treatment with Revolution. Cats already infected with adult heartworms can be given Revolution monthly to prevent further infections.

Ear Mite Treatment in Dogs and Cats

For the treatment of ear mite (O. cynotis) infestations in dogs and cats, Revolution should be administered once as a single topical dose. A second monthly dose may be required in some dogs. Monthly use of Revolution will control any subsequent ear mite infestations. In the clinical field trials ears were not cleaned, and many animals still had debris in their ears after the second dose. Cleansing of the infested ears is recommended to remove the debris.

Sarcoptic Mange Treatment in Dogs

For the treatment of sarcoptic mange (S. scabiei) in dogs, Revolution should be administered once as a single topical dose. A second monthly dose may be required in some dogs. Monthly use of Revolution will control any subsequent sarcoptic mange mite infestations. Because of the difficulty in finding sarcoptic mange mites on skin scrapings, effectiveness assessments also were based on resolution of clinical signs. Resolution of the pruritus associated with the mite infestations was observed in approximately 50% of the dogs 30 days after the first treatment and in approximately 90% of the dogs 30 days after the second monthly treatment.

Tick Control in Dogs

For the control of tick (Dermacentor variabilis) infestations in dogs, Revolution should be administered on a monthly basis. In heavy tick infestations, complete efficacy may not be achieved after the first dose. In these cases, one additional dose may be administered two weeks after the previous dose, with monthly dosing continued thereafter.

Nematode Treatment in Cats

For the treatment and control of intestinal hookworm (A. tubaeforme) and roundworm (T. cati) infections, Revolution should be applied once as a single topical dose.

WARNINGS

User Safety Warnings
Not for human use. Keep out of reach of children.
In humans, Revolution may be irritating to skin and eyes.
Reactions such as hives, itching and skin redness have been reported in humans. Individuals with known hypersensitivity to Revolution should use the product with caution or consult a health care professional. Revolution contains isopropyl alcohol and the preservative butylated hydroxytoluene (BHT).
Wash hands after use and wash off any product in contact with the skin immediately with soap and water.
If contact with eyes occurs, then flush eyes copiously with water; if wearing contact lenses, rinse the eyes first then remove contact lenses and continue to rinse for 5-10 minutes and seek medical attention.
In case of ingestion by a human, contact a physician immediately.
The safety data sheet (SDS) provides more detailed occupational safety information. To obtain a SDS contact Zoetis at 1-888-963-8471 or www.zoetisus.com.
Flammable - Keep away from heat, sparks, open flames or other sources of ignition.
Animal Safety Warnings
Do not use in sick, debilitated or underweight animals (see TARGET ANIMAL SAFETY).

PRECAUTIONS

Prior to administration of Revolution, dogs should be tested for existing heartworm infections. At the discretion of the veterinarian, infected dogs should be treated to remove adult heartworms. Revolution is not effective against adult D. immitis and, while the number of circulating microfilariae may decrease following treatment, Revolution is not effective for microfilariae clearance.
Hypersensitivity reactions have not been observed in dogs with patent heartworm infections administered Revolution (see TARGET ANIMAL SAFETY).

ADVERSE REACTIONS

Pre-approval clinical trials:

Following treatment with Revolution, transient localized alopecia with or without inflammation at or near the site of application was observed in approximately 1% of 691 treated cats. Other signs observed (≤0.5% of 1743 treated cats and dogs) included vomiting, loose stool or diarrhea with or without blood, anorexia, lethargy, salivation, tachypnea, and muscle tremors.

Post-approval experience (2021):

The following adverse events are based on post-approval adverse drug experience reporting for Revolution. Not all adverse events are reported to FDA/CVM. It is not always possible to reliably estimate the adverse event frequency or establish a causal relationship to product exposure using this data.
The following adverse events reported for dogs are listed in decreasing order of reporting frequency:
Lethargy, vomiting, diarrhea, anorexia, generalized pruritus, seizures, application site reactions (including alopecia, lesions, erythema, pruritus, and inflammation), tremors, ataxia, death, and dermatitis.
The following adverse events reported for cats are listed in decreasing order of reporting frequency:
Application site reactions (including alopecia, lesions, erythema, pruritus, inflammation, vesicles, blisters, and excoriations), lethargy, anorexia, vomiting, death, generalized pruritus, diarrhea, ataxia, fever, generalized alopecia, tremors, hypersalivation, dermatitis, and seizures.

CONTACT INFORMATION

Contact Zoetis at 1-888-963-8471 or www.zoetis.com. To report suspected adverse drug experiences, contact Zoetis at 1-888-963-8471. For additional information about reporting adverse drug experiences for animal drugs, contact FDA at 1-888-FDA-VETS or www.fda.gov/reportanimalae.

TARGET ANIMAL SAFETY

Revolution has been tested safe in over 100 different pure and mixed breeds of healthy dogs and over 15 different pure and mixed breeds of healthy cats, including pregnant and lactating females, breeding males and females, puppies six weeks of age and older, kittens eight weeks of age and older, and avermectin-sensitive collies. A kitten, estimated to be 5–6 weeks old (0.3 kg), died 8 1⁄2 hours after receiving a single treatment of Revolution at the recommended dosage. The kitten displayed clinical signs which included muscle spasms, salivation and neurological signs. The kitten was a stray with an unknown history and was malnourished and underweight (see WARNINGS).

DOGS:

In safety studies, Revolution was administered at 1, 3, 5, and 10 times the recommended dose to six-week-old puppies, and no adverse reactions were observed. The safety of Revolution administered orally also was tested in case of accidental oral ingestion. Oral administration of Revolution at the recommended topical dose in 5- to 8-month-old beagles did not cause any adverse reactions. In a pre-clinical study selamectin was dosed orally to ivermectin-sensitive collies. Oral administration of 2.5, 10, and 15 mg/kg in this dose escalating study did not cause any adverse reactions; however, eight hours after receiving 5 mg/kg orally, one avermectin-sensitive collie became ataxic for several hours, but did not show any other adverse reactions after receiving subsequent doses of 10 and 15 mg/kg orally. In a topical safety study conducted with avermectin-sensitive collies at 1, 3 and 5 times the recommended dose of Revolution, salivation was observed in all treatment groups, including the vehicle control. Revolution also was administered at 3 times the recommended dose to heartworm infected dogs, and no adverse effects were observed.

CATS:

In safety studies, Revolution was applied at 1, 3, 5, and 10 times the recommended dose to six-week-old kittens. No adverse reactions were observed. The safety of Revolution administered orally also was tested in case of accidental oral ingestion. Oral administration of the recommended topical dose of Revolution to cats caused salivation and intermittent vomiting. Revolution also was applied at 4 times the recommended dose to patent heartworm infected cats, and no adverse reactions were observed.
In well-controlled clinical studies, Revolution was used safely in animals receiving other frequently used veterinary products such as vaccines, anthelmintics, antiparasitics, antibiotics, steroids, collars, shampoos and dips.

STORAGE CONDITIONS

Store below 30°C (86°F).

HOW SUPPLIED

Available in eight separate dose strengths for dogs and cats of different weights (see DOSAGE). Revolution for puppies and kittens is available in cartons containing 3 single dose tubes. Revolution for cats and dogs is available in cartons containing 3 or 6 single dose tubes.

Approved by FDA under NADA # 141-152
Revised: July 2024
zoetis
Manufactured and Distributed by:
Zoetis Inc.
Kalamazoo, MI 49007
Product of the United Kingdom
40048985